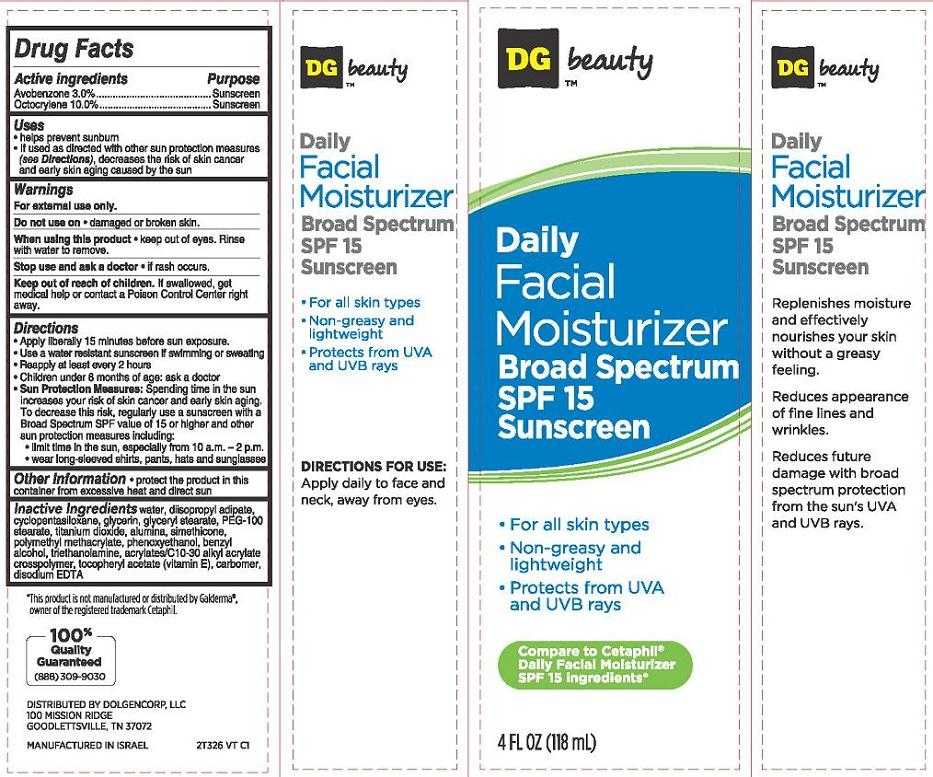 DRUG LABEL: Daily Facial Moisturizer Broad Spectrum SPF15 Sunscreen
NDC: 55910-326 | Form: CREAM
Manufacturer: Dolgencorp Inc.
Category: otc | Type: HUMAN OTC DRUG LABEL
Date: 20130715

ACTIVE INGREDIENTS: AVOBENZONE 3 g/100 mL; OCTOCRYLENE 10 g/100 mL
INACTIVE INGREDIENTS: WATER; DIISOPROPYL ADIPATE; CYCLOMETHICONE 5; GLYCERIN; GLYCERYL MONOSTEARATE; PEG-100 STEARATE; TITANIUM DIOXIDE; ALUMINUM OXIDE; SILICON DIOXIDE; METHACRYLIC ACID - METHYL METHACRYLATE COPOLYMER (1:2); PHENOXYETHANOL; BENZYL ALCOHOL; TROLAMINE; CARBOMER INTERPOLYMER TYPE A (ALLYL SUCROSE CROSSLINKED); .ALPHA.-TOCOPHEROL ACETATE; CARBOMER COPOLYMER TYPE A (ALLYL PENTAERYTHRITOL CROSSLINKED); EDETATE DISODIUM

DG™ beauty Daily Facial Moisturizer Broad Spectrum SPF15 Sunscreen

Active ingredient

Avobenzone 3.0%

Octocrylene 10.0%

Purpose

Sunscreen

Uses

- helps prevent sunburn
- If used as directed with other sun protection measures (see Directions), decreases the risk of skin cancer and early skin aging caused by the sun

Warnings

For external use only.

Do not use on

- damaged or broken skin.

When using this product

- keep out of eyes. Rinse with water to remove.

Stop use and ask a doctor

- if rash occurs.

Keep Out of Reach of Children.

If swallowed, get medical help or contact a Poison Control Center right away.

Directions

- Apply liberally 15 minutes before sun exposure.
- Use a water resistant sunscreen if swimming or sweating
- Reapply at least every 2 hours
- Children under 6 months of age: ask a doctor
- Sun Protection Measures: Spending time in the sun increases your risk of skin cancer and early skin aging. To decrease this risk, regularly use a sunscree with a Broad Spectrum SPF value of 15 or higher and other sun protection measures including:
  - limit time in the sun, especially from 10 a.m. - 2 p.m.
  - wear long-sleeved shirts, pants, hats and sunglasses

Other Information

- protect the product in this container from excessive heat and direct sun

Inactive Ingredients

water, disopropyl adipate, cyclopentasiloxane, glycerin, glyceryl stearate, PEG-100 stearate, titanium dioxide, alumina, simethicone, polymethyl methacrylate, phenoxyethanol, benzyl alcohol, triethanolamine, acrylates/C10-30 alkyl acrylate crosspolymer, tocopheryl acetate (vitamin E), carbomer, disodium EDTA

Package/Label Principal Display Panel

DG™ beauty Daily Facial Moisturizer Broad Spectrum SPF 15 Sunscreen

- For all skin types
- Non-greasy and lightweight
- Protects from UVA and UVB rays

Compare to Cetaphil®
Daily Facial Moisturizer SPF 15 ingredients*

4 FL OZ (118 mL)

*This product is not manufactured or distributed by Galderma®, owner of the registered trademark Cetaphil.

DISTRIBUTED BY:
DOLGENCORP, LLC
100 MISSION RIDGE
GOODLETTSVILLE, TN 37072
MANUFACTURED IN ISRAEL
2T326 VT C1

Carton Label